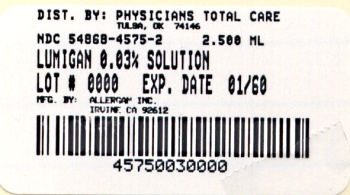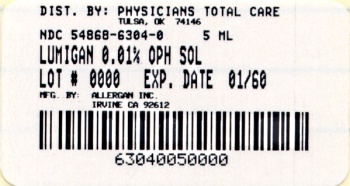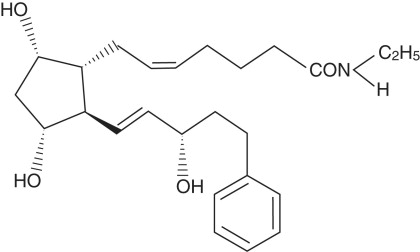 DRUG LABEL: LUMIGAN
NDC: 54868-6304 | Form: SOLUTION/ DROPS
Manufacturer: Physicians Total Care, Inc.
Category: prescription | Type: HUMAN PRESCRIPTION DRUG LABEL
Date: 20100831

ACTIVE INGREDIENTS: bimatoprost 0.1 mg/1 mL
INACTIVE INGREDIENTS: sodium chloride; benzalkonium chloride; sodium phosphate, dibasic; citric acid monohydrate; water; Sodium hydroxide; hydrochloric acid

HIGHLIGHTS OF PRESCRIBING INFORMATION

These highlights do not include all the information needed to use LUMIGAN® 0.01% and 0.03% (bimatoprost ophthalmic solution) safely and effectively. See full prescribing information for LUMIGAN®.
LUMIGAN® 0.01% and 0.03% (bimatoprost ophthalmic solution)
Initial U.S. Approval: 2001

1 INDICATIONS AND USAGE

LUMIGAN® is a prostaglandin analog indicated for the reduction of elevated intraocular pressure in patients with open angle glaucoma or ocular hypertension. (1)

2 DOSAGE AND ADMINISTRATION

One drop in the affected eye(s) once daily in the evening. (2)

3 DOSAGE FORMS AND STRENGTHS

Solution containing 0.1 mg/mL bimatoprost (LUMIGAN® 0.01%) or containing 0.3 mg/mL bimatoprost (LUMIGAN® 0.03%). (3)

5 WARNINGS AND PRECAUTIONS

- Pigmentation.
  Pigmentation of the iris, periorbital tissue (eyelid) and eyelashes can occur. Iris pigmentation is likely to be permanent (5.1).
- Eyelash Changes.
  Gradual change to eyelashes including increased length, thickness and number of lashes. Usually reversible. (5.2)

6 ADVERSE REACTIONS

Most common adverse reaction (range 25% - 45%) is conjunctival hyperemia. (6.1)

To report SUSPECTED ADVERSE REACTIONS, contact Allergan at 1-800-433-8871 or FDA at 1-800-FDA-1088 or www.fda.gov/medwatch.

8 USE IN SPECIFIC POPULATIONS

Use in pediatric patients below the age of 16 years is not recommended because of potential safety concerns related to increased pigmentation following long-term chronic use. (8.4)

FULL PRESCRIBING INFORMATION

1 INDICATIONS AND USAGE

LUMIGAN® 0.01% and 0.03% (bimatoprost ophthalmic solution) is indicated for the reduction of elevated intraocular pressure in patients with open angle glaucoma or ocular hypertension.

2 DOSAGE AND ADMINISTRATION

The recommended dosage is one drop in the affected eye(s) once daily in the evening. LUMIGAN® 0.01% and 0.03% (bimatoprost ophthalmic solution) should not be administered more than once daily since it has been shown that more frequent administration of prostaglandin analogs may decrease the intraocular pressure lowering effect.

Reduction of the intraocular pressure starts approximately 4 hours after the first administration with maximum effect reached within approximately 8 to 12 hours.

LUMIGAN® may be used concomitantly with other topical ophthalmic drug products to lower intraocular pressure. If more than one topical ophthalmic drug is being used, the drugs should be administered at least five (5) minutes apart.

3 DOSAGE FORMS AND STRENGTHS

Ophthalmic solution containing bimatoprost 0.1 mg/mL (LUMIGAN® 0.01%) or containing bimatoprost 0.3 mg/mL (LUMIGAN® 0.03%).

4 CONTRAINDICATIONS

None

5 WARNINGS AND PRECAUTIONS

5.1 Pigmentation

Bimatoprost ophthalmic solution has been reported to cause changes to pigmented tissues. The most frequently reported changes have been increased pigmentation of the iris, periorbital tissue (eyelid) and eyelashes. Pigmentation is expected to increase as long as bimatoprost is administered. The pigmentation change is due to increased melanin content in the melanocytes rather than to an increase in the number of melanocytes. After discontinuation of bimatoprost, pigmentation of the iris is likely to be permanent, while pigmentation of the periorbital tissue and eyelash changes have been reported to be reversible in some patients. Patients who receive treatment should be informed of the possibility of increased pigmentation. The long term effects of increased pigmentation are not known.

Iris color change may not be noticeable for several months to years. Typically, the brown pigmentation around the pupil spreads concentrically towards the periphery of the iris and the entire iris or parts of the iris become more brownish. Neither nevi nor freckles of the iris appear to be affected by treatment. While treatment with LUMIGAN® 0.01% and 0.03% (bimatoprost ophthalmic solution) can be continued in patients who develop noticeably increased iris pigmentation, these patients should be examined regularly. (see PATIENT COUNSELING INFORMATION, 17.1).

5.2 Eyelash Changes

LUMIGAN® 0.01% and 0.03% may gradually change eyelashes and vellus hair in the treated eye. These changes include increased length, thickness, and number of lashes. Eyelash changes are usually reversible upon discontinuation of treatment.

5.3 Intraocular Inflammation

LUMIGAN® 0.01% and 0.03% should be used with caution in patients with active intraocular inflammation (e.g., uveitis) because the inflammation may be exacerbated.

5.4 Macular Edema

Macular edema, including cystoid macular edema, has been reported during treatment with bimatoprost ophthalmic solution. LUMIGAN® 0.01% and 0.03% should be used with caution in aphakic patients, in pseudophakic patients with a torn posterior lens capsule, or in patients with known risk factors for macular edema.

5.5 Angle-closure, Inflammatory, or Neovascular Glaucoma

LUMIGAN® 0.01% and 0.03% has not been evaluated for the treatment of angle-closure, inflammatory or neovascular glaucoma.

5.6 Bacterial Keratitis

There have been reports of bacterial keratitis associated with the use of multiple-dose containers of topical ophthalmic products. These containers had been inadvertently contaminated by patients who, in most cases, had a concurrent corneal disease or a disruption of the ocular epithelial surface (see PATIENT COUNSELING INFORMATION, 17.3).

5.7 Use with Contact Lenses

Contact lenses should be removed prior to instillation of LUMIGAN® 0.01% and 0.03% and may be reinserted 15 minutes following its administration.

6 ADVERSE REACTIONS

6.1 Clinical Studies Experience

Because clinical studies are conducted under widely varying conditions, adverse reaction rates observed in the clinical studies of a drug cannot be directly compared to rates in the clinical studies of another drug and may not reflect the rates observed in practice.

In clinical studies with bimatoprost ophthalmic solutions (0.01% or 0.03%) the most common adverse event was conjunctival hyperemia (range 25% – 45%). Approximately 0.5% to 3% of patients discontinued therapy due to conjunctival hyperemia with 0.01% or 0.03% bimatoprost ophthalmic solutions. Other common events (>10%) included growth of eyelashes, and ocular pruritus.

Additional ocular adverse events (reported in 1 to 10% of patients) with bimatoprost ophthalmic solutions included ocular dryness, visual disturbance, ocular burning, foreign body sensation, eye pain, pigmentation of the periocular skin, blepharitis, cataract, superficial punctate keratitis, eyelid erythema, ocular irritation, eyelash darkening, eye discharge, tearing, photophobia, allergic conjunctivitis, asthenopia, increases in iris pigmentation, conjunctival edema, conjunctival hemorrhage, and abnormal hair growth. Intraocular inflammation, reported as iritis was reported in less than 1% of patients.

Systemic adverse events reported in approximately 10% of patients with bimatoprost ophthalmic solutions were infections (primarily colds and upper respiratory tract infections). Other systemic adverse events (reported in 1 to 5% of patients) included headaches, abnormal liver function tests, and asthenia.

8 USE IN SPECIFIC POPULATIONS

8.1 Pregnancy

Pregnancy Category C

TERATOGENIC EFFECTS

Teratogenic effects: In embryo/fetal developmental studies in pregnant mice and rats, abortion was observed at oral doses of bimatoprost which achieved at least 33 or 97 times, respectively, the maximum intended human exposure based on blood AUC levels.

At doses at least 41 times the maximum intended human exposure based on blood AUC levels, the gestation length was reduced in the dams, the incidence of dead fetuses, late resorptions, peri- and postnatal pup mortality was increased, and pup body weights were reduced.

There are no adequate and well-controlled studies of LUMIGAN® 0.01% and 0.03% (bimatoprost ophthalmic solution) administration in pregnant women. Because animal reproductive studies are not always predictive of human response LUMIGAN® should be administered during pregnancy only if the potential benefit justifies the potential risk to the fetus.

8.3 Nursing Mothers

It is not known whether LUMIGAN® 0.01% and 0.03% is excreted in human milk, although in animal studies, bimatoprost has been shown to be excreted in breast milk. Because many drugs are excreted in human milk, caution should be exercised when LUMIGAN® is administered to a nursing woman.

8.4 Pediatric Use

Use in pediatric patients below the age of 16 years is not recommended because of potential safety concerns related to increased pigmentation following long-term chronic use.

8.5 Geriatric Use

No overall clinical differences in safety or effectiveness have been observed between elderly and other adult patients.

8.6 Hepatic Impairment

In patients with a history of liver disease or abnormal ALT, AST and/or bilirubin at baseline, bimatoprost 0.03% had no adverse effect on liver function over 48 months.

10 OVERDOSAGE

No information is available on overdosage in humans. If overdose with LUMIGAN® 0.01% and 0.03% (bimatoprost ophthalmic solution) occurs, treatment should be symptomatic.

In oral (by gavage) mouse and rat studies, doses up to 100 mg/kg/day did not produce any toxicity. This dose expressed as mg/m^2 is at least 70 times higher than the accidental dose of one bottle of LUMIGAN® 0.03% for a 10 kg child.

11 DESCRIPTION

LUMIGAN® 0.01% and 0.03% (bimatoprost ophthalmic solution) is a synthetic prostamide analog with ocular hypotensive activity. Its chemical name is (Z)-7-[(1R,2R,3R,5S)-3,5-Dihydroxy-2-[(1E,3S)-3-hydroxy-5-phenyl-1-pentenyl]cyclopentyl]-5-N-ethylheptenamide, and its molecular weight is 415.58. Its molecular formula is C25H37NO4. Its chemical structure is:

Bimatoprost is a powder, which is very soluble in ethyl alcohol and methyl alcohol and slightly soluble in water. LUMIGAN® 0.01% and 0.03% is a clear, isotonic, colorless, sterile ophthalmic solution with an osmolality of approximately 290 mOsmol/kg.

LUMIGAN® 0.01% contains Active: bimatoprost 0.1 mg/mL; Preservative: benzalkonium chloride 0.2 mg/mL; Inactives: sodium chloride; sodium phosphate, dibasic; citric acid; and purified water. Sodium hydroxide and/or hydrochloric acid may be added to adjust pH. The pH during its shelf life ranges from 6.8-7.8.

LUMIGAN® 0.03% contains Active: bimatoprost 0.3 mg/mL; Preservative: benzalkonium chloride 0.05 mg/mL; Inactives: sodium chloride; sodium phosphate, dibasic; citric acid; and purified water. Sodium hydroxide and/or hydrochloric acid may be added to adjust pH. The pH during its shelf life ranges from 6.8-7.8.

12 CLINICAL PHARMACOLOGY

12.1 Mechanism of Action

Bimatoprost, a prostaglandin analog, is a synthetic structural analog of prostaglandin with ocular hypotensive activity. It selectively mimics the effects of naturally occurring substances, prostamides. Bimatoprost is believed to lower intraocular pressure (IOP) in humans by increasing outflow of aqueous humor through both the trabecular meshwork and uveoscleral routes. Elevated IOP presents a major risk factor for glaucomatous field loss. The higher the level of IOP, the greater the likelihood of optic nerve damage and visual field loss.

12.3 Pharmacokinetics

Absorption: After one drop of bimatoprost ophthalmic solution 0.03% was administered once daily to both eyes of 15 healthy subjects for two weeks, blood concentrations peaked within 10 minutes after dosing and were below the lower limit of detection (0.025 ng/mL) in most subjects within 1.5 hours after dosing. Mean Cmax and AUC0-24hr values were similar on days 7 and 14 at approximately 0.08 ng/mL and 0.09 ng•hr/mL, respectively, indicating that steady state was reached during the first week of ocular dosing. There was no significant systemic drug accumulation over time.

Distribution: Bimatoprost is moderately distributed into body tissues with a steady-state volume of distribution of 0.67 L/kg. In human blood, bimatoprost resides mainly in the plasma. Approximately 12% of bimatoprost remains unbound in human plasma.

Metabolism: Bimatoprost is the major circulating species in the blood once it reaches the systemic circulation following ocular dosing. Bimatoprost then undergoes oxidation, N-deethylation and glucuronidation to form a diverse variety of metabolites.

Elimination: Following an intravenous dose of radiolabeled bimatoprost (3.12 μg/kg) to six healthy subjects, the maximum blood concentration of unchanged drug was 12.2 ng/mL and decreased rapidly with an elimination half-life of approximately 45 minutes. The total blood clearance of bimatoprost was 1.5 L/hr/kg. Up to 67% of the administered dose was excreted in the urine while 25% of the dose was recovered in the feces.

13 NONCLINICAL TOXICOLOGY

13.1 Carcinogenesis, Mutagenesis, Impairment of Fertility

Bimatoprost was not carcinogenic in either mice or rats when administered by oral gavage at doses of up to 2 mg/kg/day and 1 mg/kg/day respectively (at least 192 and 291 times the recommended human exposure based on blood AUC levels respectively) for 104 weeks.

Bimatoprost was not mutagenic or clastogenic in the Ames test, in the mouse lymphoma test, or in the in vivo mouse micronucleus tests.

Bimatoprost did not impair fertility in male or female rats up to doses of 0.6 mg/kg/day (at least 103 times the recommended human exposure based on blood AUC levels).

14 CLINICAL STUDIES

In clinical studies of patients with open angle glaucoma or ocular hypertension with a mean baseline IOP of 26 mmHg, the IOP-lowering effect of LUMIGAN® 0.03% (bimatoprost ophthalmic solution) once daily (in the evening) was 7-8 mmHg.

In a 3 month clinical study of patients with open angle glaucoma or ocular hypertension with an average baseline IOP of 23.5 mmHg, the IOP-lowering effect of LUMIGAN® 0.01% once daily (in the evening) was up to 7.5 mmHg and was approximately 0.5 mmHg less effective than LUMIGAN® 0.03%. In this same study, LUMIGAN® 0.01% also had a similar overall safety profile compared with LUMIGAN® 0.03%. After 12 months of treatment, discontinuations were 8.1% for LUMIGAN® 0.01% and 13.4% for LUMIGAN® 0.03%.

16 HOW SUPPLIED/STORAGE AND HANDLING

LUMIGAN® (bimatoprost ophthalmic solution) 0.01% is supplied sterile in opaque white low density polyethylene ophthalmic dispenser bottles and tips with turquoise polystyrene caps in the following sizes:

5 mL fill - NDC 54868-6304-0

LUMIGAN® (bimatoprost ophthalmic solution) 0.03% is supplied sterile in opaque white low density polyethylene ophthalmic dispenser bottles and tips with turquoise polystyrene caps in the following sizes:

2.5 mL fill - NDC 54868-4575-2
5 mL fill - NDC 54868-4575-0
7.5 mL fill - NDC 54868-4575-1

STORAGE AND HANDLING

Storage: LUMIGAN® 0.01% and 0.03% should be stored at 2° to 25°C (36° to 77°F).

17 PATIENT COUNSELING INFORMATION

17.1 Potential for Pigmentation

Patients should be advised about the potential for increased brown pigmentation of the iris, which may be permanent. Patients should also be informed about the possibility of eyelid skin darkening, which may be reversible after discontinuation of LUMIGAN® 0.01% and 0.03% (bimatoprost ophthalmic solution).

17.2 Potential for Eyelash Changes

Patients should also be informed of the possibility of eyelash and vellus hair changes in the treated eye during treatment with LUMIGAN® 0.01% and 0.03%. These changes may result in a disparity between eyes in length, thickness, pigmentation, number of eyelashes or vellus hairs, and/or direction of eyelash growth. Eyelash changes are usually reversible upon discontinuation of treatment.

17.3 Handling the Container

Patients should be instructed to avoid allowing the tip of the dispensing container to contact the eye, surrounding structures, fingers, or any other surface in order to avoid contamination of the solution by common bacteria known to cause ocular infections. Serious damage to the eye and subsequent loss of vision may result from using contaminated solutions.

17.4 When to Seek Physician Advice

Patients should also be advised that if they develop an intercurrent ocular condition (e.g., trauma or infection), have ocular surgery, or develop any ocular reactions, particularly conjunctivitis and eyelid reactions, they should immediately seek their physician's advice concerning the continued use of LUMIGAN® 0.01% and 0.03%.

17.5 Use with Contact Lenses

Patients should be advised that LUMIGAN® 0.01% and 0.03% contains benzalkonium chloride, which may be absorbed by soft contact lenses. Contact lenses should be removed prior to instillation of LUMIGAN® and may be reinserted 15 minutes following its administration.

17.6 Use with Other Ophthalmic Drugs

If more than one topical ophthalmic drug is being used, the drugs should be administered at least five (5) minutes between applications.

© 2010 Allergan, Inc.
Irvine, CA 92612
® marks owned by Allergan, Inc.
U.S. Patents 5,688,819 and 6,403,649

71807US12B
Relabeling of additional barcode by:
Physicians Total Care, Inc.
Tulsa, OK 74146

PACKAGE LABEL

NDC 54868-6304-0

LUMIGAN®

(bimatoprost

ophthalmic solution)

0.01%

Rx only

5 mL sterile

PACKAGE LABEL

NDC 54868-4575-2

LUMIGAN®

(bimatoprost

ophthalmic solution)

0.03%

Rx only

2.5 mL sterile